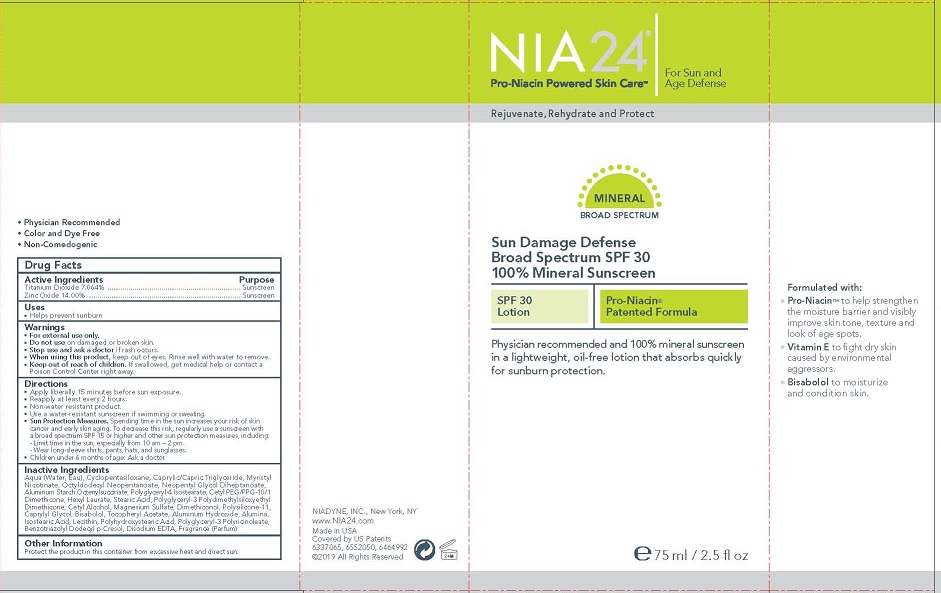 DRUG LABEL: NIA24 SUN DAMAGE DEFENSE BROAD SPECTRUM 100 PERCENT MINERAL SUNSCREEN
NDC: 43115-101 | Form: LOTION
Manufacturer: NIADYNE INC
Category: otc | Type: HUMAN OTC DRUG LABEL
Date: 20181226

ACTIVE INGREDIENTS: TITANIUM DIOXIDE 7.1 g/100 mL; ZINC OXIDE 14 g/100 mL
INACTIVE INGREDIENTS: WATER; CYCLOMETHICONE 5; MEDIUM-CHAIN TRIGLYCERIDES; MYRISTYL NICOTINATE; OCTYLDODECYL NEOPENTANOATE; NEOPENTYL GLYCOL DIHEPTANOATE; ALUMINUM STARCH OCTENYLSUCCINATE; POLYGLYCERYL-4 ISOSTEARATE; CETYL PEG/PPG-10/1 DIMETHICONE (HLB 1.5); HEXYL LAURATE; STEARIC ACID; POLYGLYCERYL-3 POLYDIMETHYLSILOXYETHYL DIMETHICONE (4000 MPA.S); CETYL ALCOHOL; MAGNESIUM SULFATE ANHYDROUS; DIMETHICONOL (14000 CST); POLYSILICONE-15; CAPRYLYL GLYCOL; .ALPHA.-BISABOLOL, (+)-; .ALPHA.-TOCOPHEROL ACETATE; ALUMINUM HYDROXIDE; ALUMINUM OXIDE; ISOSTEARIC ACID; LECITHIN, SOYBEAN; POLYHYDROXYSTEARIC ACID (2300 MW); POLYGLYCERYL-3 RICINOLEATE; BENZOTRIAZOLYL DODECYL P-CRESOL; EDETATE DISODIUM

NIA24 SUN DAMAGE DEFENSE BROAD SPECTRUM SPF 30 100% MINERAL SUNSCREEN

Active Ingredients

TITANIUM DIOXIDE 7.064%

ZINC OXIDE 14.00%

Purpose

Sunscreen

Warnings

- For external use only.
- Do not use on damaged or broken skin.
- Stop use and ask a doctor if rash occurs.
- When using this product, keep out of eyes. Rinse well with water to remove.

Keep out of reach of children. If swallowed, get medical help or contact a Poison Control Center right away.

Directions

- Apply liberally 15 minutes before sun exposure.
- Reapply at least every 2 hours.
- Non-water resistant product.
- Use a water-resistant sunscreen if swimming or sweating.
- Sun Protection Measures. Spending time in the sun increases your risk of skin cancer and early skin aging. To decrease this risk, regularly use a sunscreen witha broad spectrum SPF 15 or higher and other sun protection measures, including:
  - Limit time in the sun, especially from 10 am – 2 pm.
  - Wear long-sleeve shirts, pants, hats, and sunglasses.
- Children under 6 months of age: Ask a doctor.

Other information

Protect the product in this container from excessive heat and direct sun.

Inactive Ingredients

Nicotinate, Octyldodecyl Neopentanoate, Neopentyl Glycol Diheptanoate, Aluminum Starch Octenylsuccinate, Polyglyceryl-4 Isostearate, Cetyl PEG/PPG-10/1 Dimethicone, Hexyl Laurate, Stearic Acid, Polyglyceryl-3 Polydimethylsiloxyethyl Dimethicone, Cetyl Alcohol, Magnesium Sulfate, Dimethiconol, Polysilicone-11, Caprylyl Glycol, Bisabolol, Tocopheryl Acetate, Aluminum Hydroxide, Alumina,
Isostearic Acid, Lecithin, Polyhydroxystearic Acid, Polyglyceryl-3 Polyricinoleate, Benzotriazolyl Dodecyl p-Cresol, Disodium EDTA, Fragrance (Parfum)